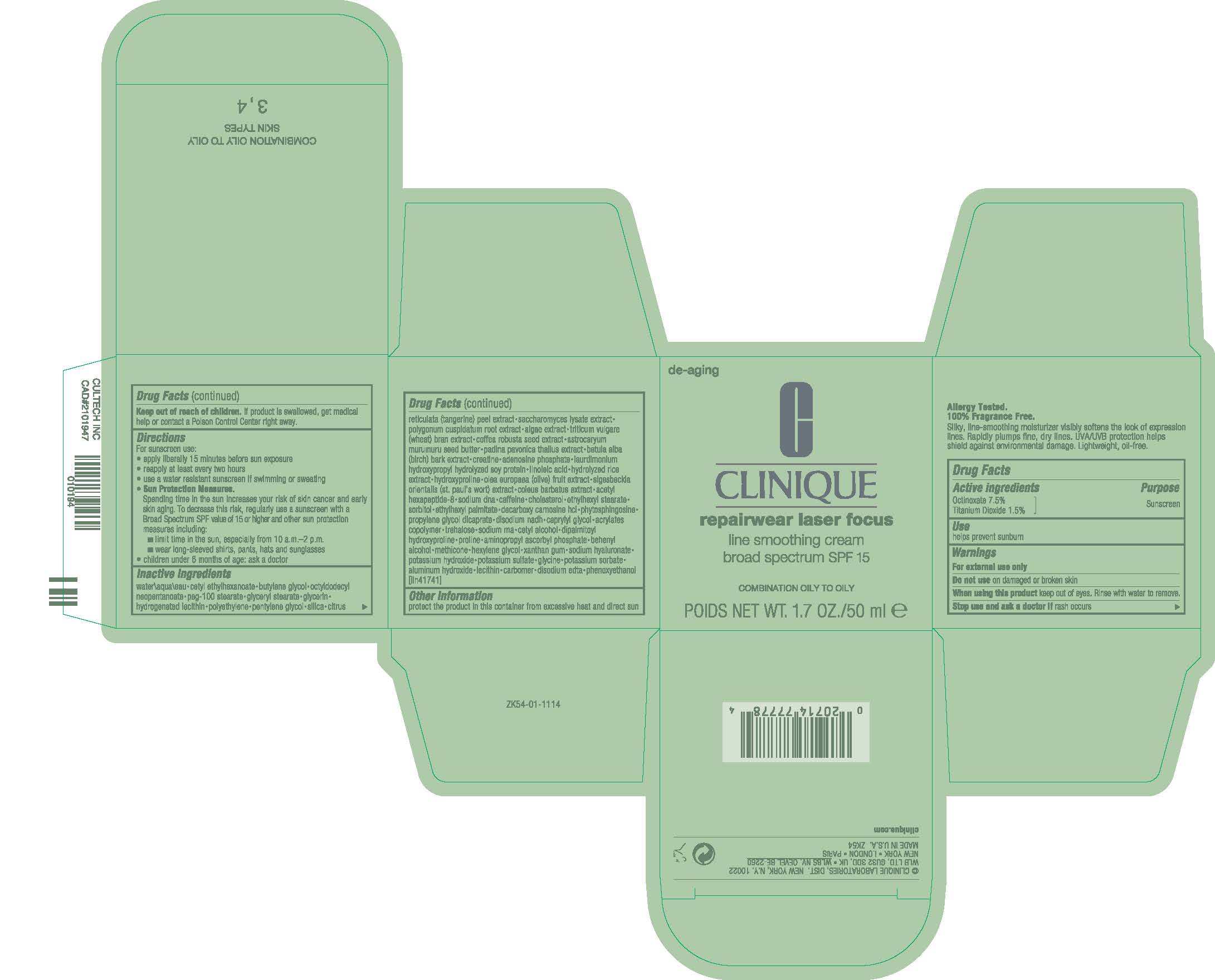 DRUG LABEL: REPAIRWEAR LASER FOCUS SPF 15 LINE SMOOTHING CO/O
NDC: 49527-118 | Form: CREAM
Manufacturer: CLINIQUE LABORATORIES LLC
Category: otc | Type: HUMAN OTC DRUG LABEL
Date: 20240209

ACTIVE INGREDIENTS: OCTINOXATE 75 mg/1 mL; TITANIUM DIOXIDE 15 mg/1 mL
INACTIVE INGREDIENTS: DISODIUM NICOTINAMIDE ADENINE DINUCLEOTIDE; CAPRYLYL GLYCOL; BUTYL ACRYLATE/METHYL METHACRYLATE/METHACRYLIC ACID COPOLYMER (18000 MW); METHICONE (20 CST); HEXYLENE GLYCOL; POTASSIUM SORBATE; LINOLEIC ACID; CAFFEINE; DIPALMITOYL HYDROXYPROLINE; HYALURONATE SODIUM; DOCOSANOL; EDETATE DISODIUM ANHYDROUS; HYDROXYPROLINE; GLYCINE; HIGH DENSITY POLYETHYLENE; TANGERINE PEEL; SACCHAROMYCES LYSATE; POLYGONUM CUSPIDATUM ROOT; BUTYLENE GLYCOL; GLYCERIN; PADINA PAVONICA; CREATINE; PEG-100 STEARATE; GLYCERYL MONOSTEARATE; ADENOSINE PHOSPHATE; COLEUS BARBATUS ROOT; PHYTOSPHINGOSINE; CETYL ETHYLHEXANOATE; HYDROGENATED SOYBEAN LECITHIN; PORPHYRIDIUM PURPUREUM; WHEAT BRAN; BETULA PUBESCENS BARK; BLACK OLIVE; SIGESBECKIA ORIENTALIS FLOWERING TOP; ACETYL HEXAPEPTIDE-8; CHOLESTEROL; ETHYLHEXYL STEARATE; ETHYLHEXYL PALMITATE; DECARBOXY CARNOSINE HYDROCHLORIDE; PROLINE; POTASSIUM HYDROXIDE; POTASSIUM SULFATE; CARBOMER HOMOPOLYMER, UNSPECIFIED TYPE; SILICON DIOXIDE; ROBUSTA COFFEE BEAN; ASTROCARYUM MURUMURU SEED BUTTER; OCTYLDODECYL NEOPENTANOATE; PENTYLENE GLYCOL; WATER; PROPYLENE GLYCOL DICAPRATE; TREHALOSE; AMINOPROPYL ASCORBYL PHOSPHATE; ALUMINUM HYDROXIDE; PHENOXYETHANOL; SOYBEAN; SORBITOL; CETYL ALCOHOL; XANTHAN GUM

REPAIRWEAR LASER FOCUS SPF 15 LINE SMOOTHING CO/O

Active Ingredients

Octinoxate 7.5%
Titanium Dioxide 1.5%

Purpose

Sunscreen

Use

helps prevent sunburn

Warnings

Do not use

on damaged or broken skin

When using this product

keep out of eyes. Rinse with water to remove.

Stop use and ask a doctor if

rash occurs

Keep out of reach of children.

If product is swallowed, get medical help or contact a Poison Control Center right away.

Directions

For sunscreen use:
apply liberally 15 minutes before sun exposure
reapply at least every two hours
use a water resistant sunscreen if swimming or sweating
Sun Protection Measures.

Spending time in the sun increases your risk of skin cancer and early skin aging.

To decrease this risk, regularly use a sunscreen with a Broad Spectrum SPF value of 15 or higher and other sun protection measures including:
limit time in the sun, especially from 10 a.m.–2 p.m.
wear long-sleeved shirts, pants, hats and sunglasses
children under 6 months of age: ask a doctor

Inactive Ingredients

water\aqua\eau,cetyl ethylhexanoate,butylene glycol,octyldodecyl neopentanoate,peg-100 stearate,glyceryl stearate,glycerin,hydrogenated lecithin,polyethylene,pentylene glycol,silica,citrus reticulata (tangerine) peel extract,saccharomyces lysate extract,polygonum cuspidatum root extract,algae extract,triticum vulgare (wheat) bran extract,coffea robusta seed extract,astrocaryum murumuru seed butter,padina pavonica thallus extract,betula alba (birch) bark extract,creatine,adenosine phosphate,laurdimonium hydroxypropyl hydrolyzed soy protein,linoleic acid,hydrolyzed rice extract,hydroxyproline,olea europaea (olive) fruit extract,sigesbeckia orientalis (st. paul's wort) extract,coleus barbatus extract,acetyl hexapeptide-8,sodium dna,caffeine,cholesterol,ethylhexyl stearate,sorbitol,ethylhexyl palmitate,decarboxy carnosine hcl,phytosphingosine,propylene glycol dicaprate,disodium nadh,caprylyl glycol,acrylates copolymer,trehalose,sodium rna,cetyl alcohol,dipalmitoyl hydroxyproline,proline,aminopropyl ascorbyl phosphate,behenyl alcohol,methicone,hexylene glycol,xanthan gum,sodium hyaluronate,potassium hydroxide,potassium sulfate,glycine,potassium sorbate,aluminum hydroxide,lecithin,carbomer,disodium edta,phenoxyethanol <iln41741>

Other information

protect the product in this container from excessive heat and direct sun

PACKAGE LABEL

CLINIQUE

repairwear laser focus

line smoothing cream

braod spectrum SPF 15

COMBINATION OILY TO OILY

POIDS NET WT. 1.7 OZ/50 ml e